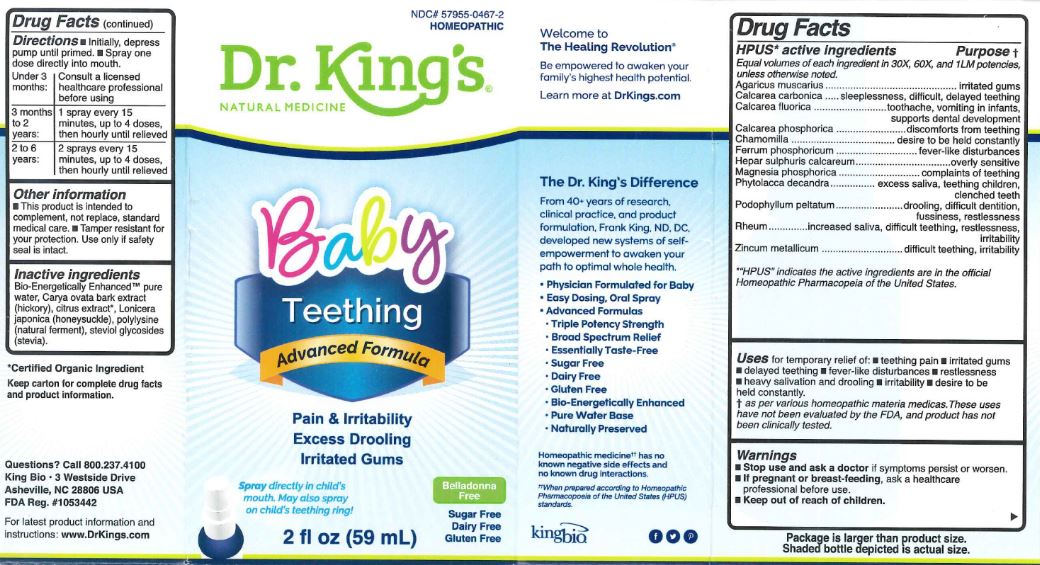 DRUG LABEL: Baby Teething
NDC: 57955-0467 | Form: LIQUID
Manufacturer: King Bio Inc
Category: homeopathic | Type: HUMAN OTC DRUG LABEL
Date: 20180305

ACTIVE INGREDIENTS: AMANITA MUSCARIA FRUITING BODY 30 [hp_X]/59 mL; OYSTER SHELL CALCIUM CARBONATE, CRUDE 30 [hp_X]/59 mL; CALCIUM FLUORIDE 30 [hp_X]/59 mL; TRIBASIC CALCIUM PHOSPHATE 30 [hp_X]/59 mL; MATRICARIA CHAMOMILLA 30 [hp_X]/59 mL; FERROSOFERRIC PHOSPHATE 30 [hp_X]/59 mL; CALCIUM SULFIDE 30 [hp_X]/59 mL; MAGNESIUM PHOSPHATE, DIBASIC TRIHYDRATE 30 [hp_X]/59 mL; PHYTOLACCA AMERICANA ROOT 30 [hp_X]/59 mL; PODOPHYLLUM 30 [hp_X]/59 mL; RHEUM OFFICINALE ROOT 30 [hp_X]/59 mL; ZINC 30 [hp_X]/59 mL
INACTIVE INGREDIENTS: WATER; CARYA OVATA BARK; CITRUS BIOFLAVONOIDS; LONICERA JAPONICA FLOWER; POLYEPSILON-LYSINE (4000 MW); REBAUDIOSIDE A

Baby Teething

HPUS Active Ingredients

Agaicus muscarius, Calcarea carbonica, Calcarea fluorica, Calcarea phosphorica, Chamomilla, Ferrum phosphoricum, Hepar sulphuris calcareum, Magnesia phosphorica, Phytolacca decandra, Podophyllum peltatum, Rheum, Zincum metallicum

Equal volumes of each in 30X, 60X, and 1LM potencies.

Purpose

HPUS Ingredient: Purpose:

Agaicus muscarius...............................irritated gums

Calcarea carbonica...............................sleeplessness, difficult, delayed teething

Calcarea fluorica..................................toothache, vomiting in infants, supports dental development

Calcarea phosphorica............................discomforts from teething

Chamomilla..........................................desire to be held constantly

Ferrum phosphoricum............................fever-like disturbaces

Hepar sulphuris calcareum......................overly sensitive

Magnesia phosphorica............................complaints of teething

Phytolacca decandra...............................excess saliva, teething children, clenched teeth

Podophyllum peltatum............................drooling, difficult dentition, fussiness, restlessness

Rheum.................................................increased saliva, difficult teething, restlessness, irritability

Zincum metallicum.................................difficult teething, irritability

Uses

for temporary relief of:

- tething pain
- irritated gums
- delayed teething
- fever-like disturbances
- restlessness
- heavy salivation and drooling
- irritability
- desire to be held constantly

Directions

- Initially, depress pump until primed.
- Spray one dose directly into mouth

Under 3 months: Consult a licensed healthcare professional before using

3 months to 2 years: 1 spray every 15 minutes. up to 4 doses, then hourly until relieved

2 to 6 years: 2 sprays every 15 minutes, up to 4 doses, then hourly until relieved

Warnings

- Stop use and ask a doctor, if symptoms persist or worsen.
- If pregnant or breast-feeding, ask a healthcare professional before use.

- Keep out of reach of children

Other Information

- This product is intended to compliment, not replace, standard medical care.
- Tamper resistant for your protection. Use only if safety seal is intact.

Inactive Ingredients

Bio-Energetically Enhanced pure water, Carya ovata bark extract (hickory), citrus extract, Lonicer japonica (honeysuckle), polylysine (natural ferment), steviol glycosides (stevia)